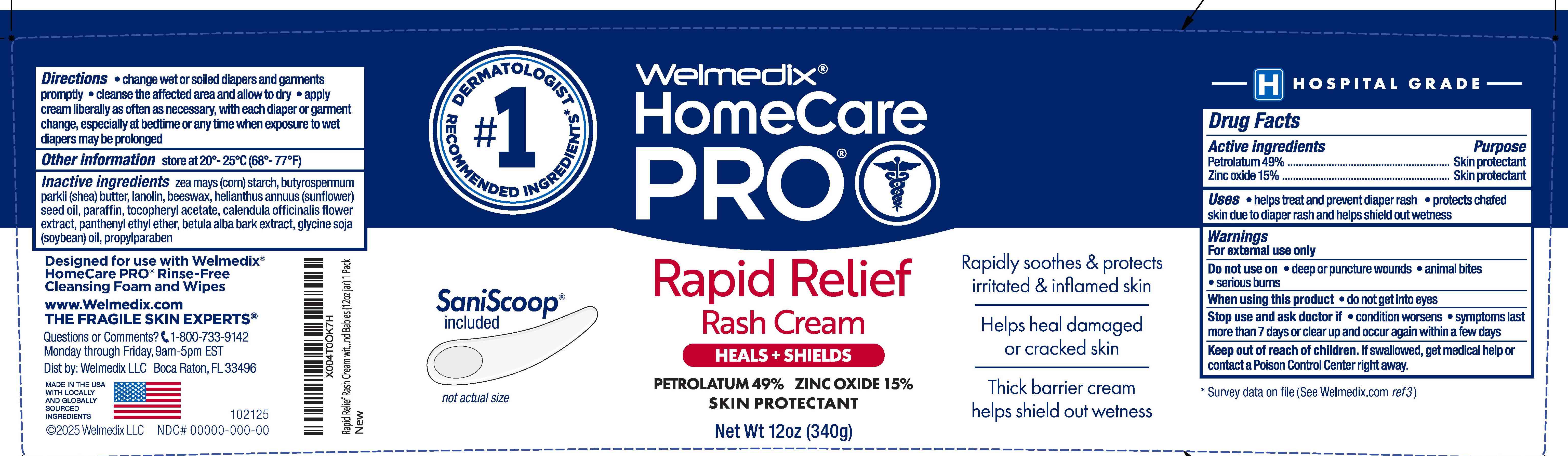 DRUG LABEL: Welmedix HomeCare PRO Rapid Relief Rash Cream
NDC: 24330-414 | Form: CREAM
Manufacturer: Welmedix LLC
Category: otc | Type: HUMAN OTC DRUG LABEL
Date: 20251114

ACTIVE INGREDIENTS: PETROLATUM 49 g/100 g; ZINC OXIDE 15 g/100 g
INACTIVE INGREDIENTS: BUTYROSPERMUM PARKII (SHEA) BUTTER; LANOLIN; BEESWAX; HELIANTHUS ANNUUS (SUNFLOWER) SEED OIL; PARAFFIN; .ALPHA.-TOCOPHEROL ACETATE; CALENDULA OFFICINALIS FLOWER; PANTHENYL ETHYL ETHER; BETULA PUBESCENS BARK; ZEA MAYS (CORN) STARCH; GLYCINE SOJA (SOYBEAN) OIL UNSAPONIFIABLES; PROPYLPARABEN

Welmedix®HomeCare PRO Rapid Relief Rash Cream

Active ingredients

Petrolatum 49%
Zinc Oxide 15%

Purpose

Skin Protectant

Uses

- Protects against minor skin irritation due to diaper rash and helps seal out wetness
- Helps treat and prevent diaper rash

Warnings

For external use only

When using this product do not get into eyes

Stop use and ask doctor if

- condition worsens
- symptoms last more than 7 days or clear up and occur again within a few days

Keep out of reach of children.

If swallowed, get medical help or contact a Poison Control Center right away.

Directions:

• Change wet and soiled diapers, garments and linens promptly • Cleanse the affected area and allow to dry • Apply cream liberally, as often as necessary, with each diaper, garment or linen change, especially at bedtime or any time when exposure to wet or soiled diapers, garments, linens, feces or urine may be prolonged

Other Information:

Store at 20-25° C (68-77° F)

Inactive ingredients

zea mays (corn) starch, butyrospermum parkii (shea) butter, lanolin, beeswax, helianthus annuus (sunflower) seed oil, paraffin, tocopheryl acetate, calendula officinalis flower extract, panthenyl ethyl ether, betula alba bark extract, glycine soja (soybean) oil, propylparaben

Principal Display Panel Tube

Welmedix®HomeCare

PRO

RAPID RELIEF
RASH CREAM

PETROLATUM 49%
ZINC OXIDE 15%

Heals + Shields

Net Wt 12 oz (340g)